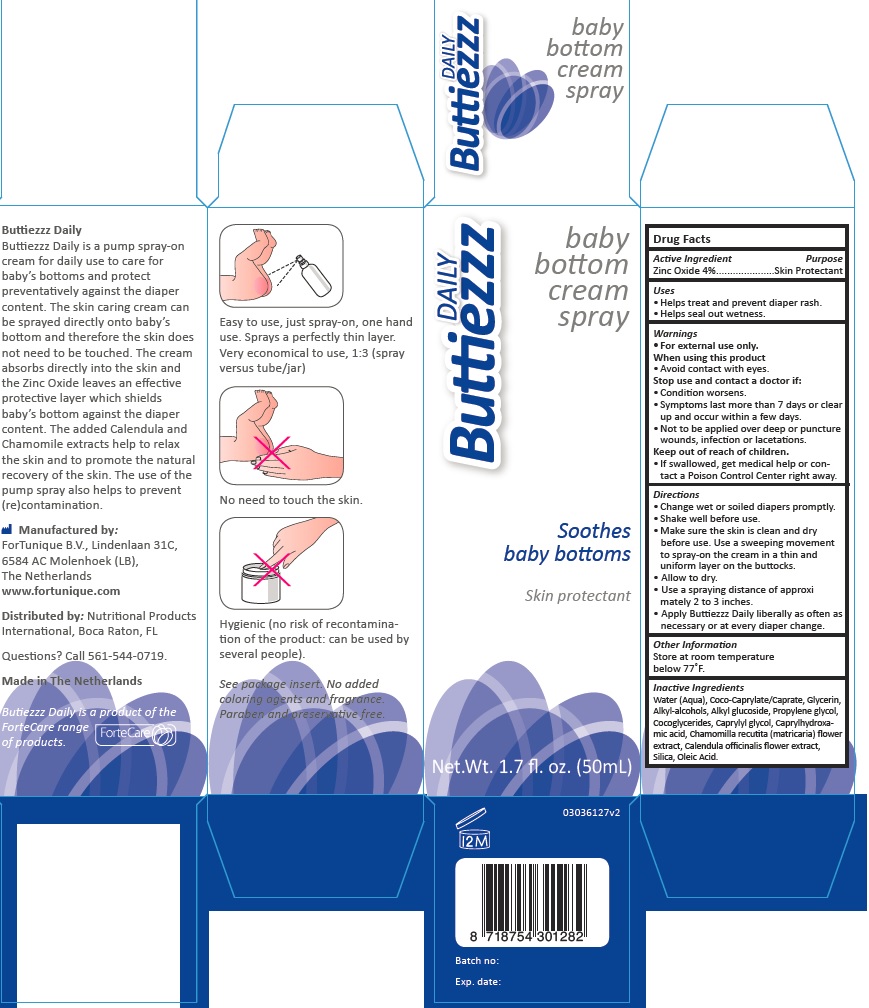 DRUG LABEL: Buttiezzz Daily
NDC: 70359-4101 | Form: SPRAY
Manufacturer: Fortunique B.V.
Category: otc | Type: HUMAN OTC DRUG LABEL
Date: 20161214

ACTIVE INGREDIENTS: ZINC OXIDE 4 g/100 g
INACTIVE INGREDIENTS: CAPRYLHYDROXAMIC ACID; C12-20 ALKYL GLUCOSIDE; C14-22 ALCOHOLS; CAPRYLYL GLYCOL; CALENDULA OFFICINALIS FLOWER; PROPYLENE GLYCOL; COCO-GLYCERIDES; WATER; GLYCERIN; OLEIC ACID; SILICON DIOXIDE; COCO-CAPRYLATE/CAPRATE; CHAMOMILE

Active Ingredients

Zinc Oxide 4%

Purpose

Skin protectant

Uses

Helps treat and prevent diaper rash

Helps seal out wetness

Warning

For external use only

When using this product

Avoid contact with eyes

Stop use and contact a Doctor if:

Condition worsens

Symptoms last more than 7 days or clear up and occur again within a few days

Not to be applied over deep or puncture wound, infection or lacerations

Keep out of reach of children

If swallowed, get medical help or contact a Poison Control Center right away

Directions

Change wet or soiled diapers promptly

Shake well before use

Make sure the skin is clean and dry before use.Use a sweeping movement to spray-on the cream in a thin and uniform layer on the buttocks

Allow to dry

Use a spraying distance approximately 2 to 3 inches

Apply Buttiezzz Daily liberally as often as necessary or at every diaper change

Other information

Store at room temperature below 77º F

Inactive Ingredients

Water(Aqua)

Coco-Caprylate/Caprate

Glycerin

Alkyl- Alcohols

Alkyl Glucoside

Propylene glycol

Cocoglycerides

Caprylyl Glycol

Capryl-Hidroxamic acid

Chamomilla Recutita(Matricaria)Flower Extract

Calendula Officinalis Flower Extract

Silica

Oleic Acid